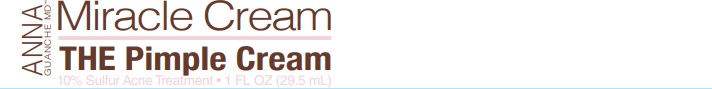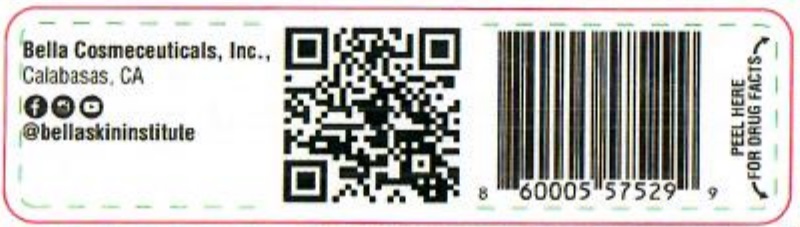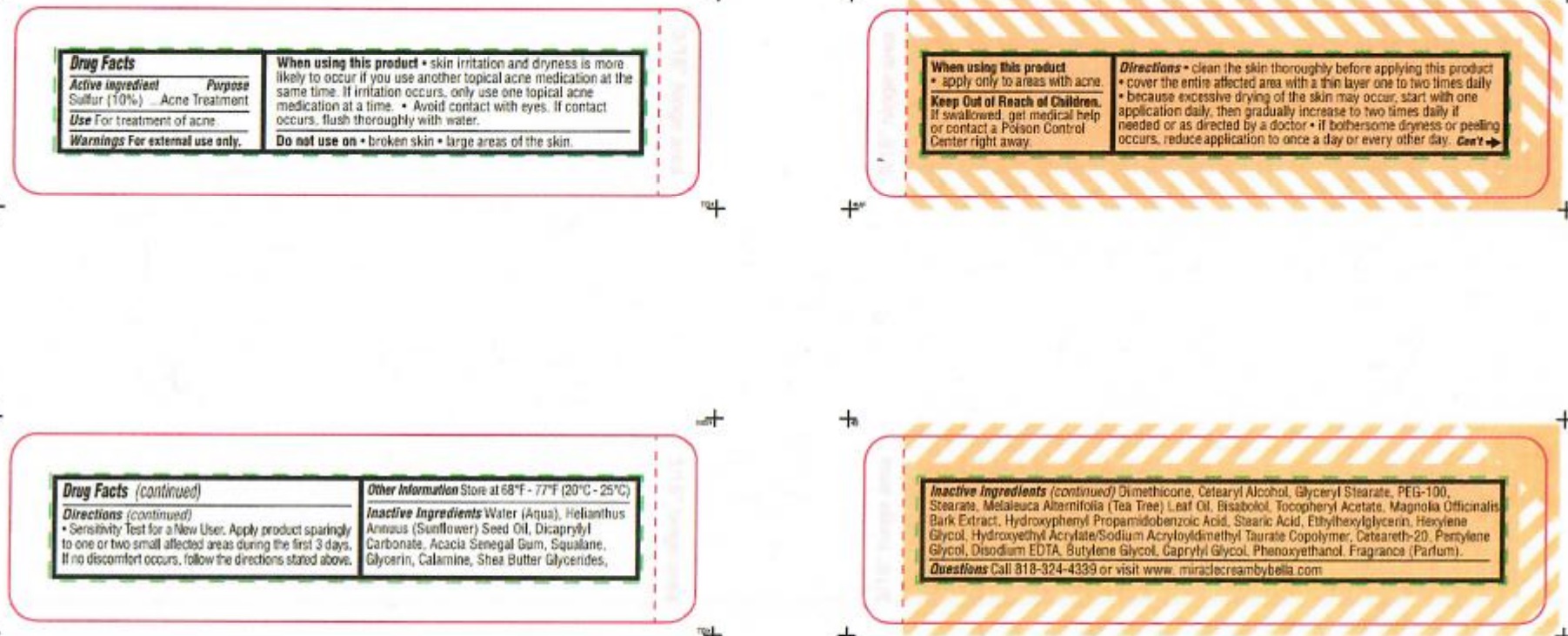 DRUG LABEL: Anna Guanche MD Miracle Cream The Pimple Cream
NDC: 80841-100 | Form: CREAM
Manufacturer: Bella Cosmeceuticals, Inc.
Category: otc | Type: HUMAN OTC DRUG LABEL
Date: 20251130

ACTIVE INGREDIENTS: SULFUR 100 mg/1 mL
INACTIVE INGREDIENTS: BUTYLENE GLYCOL; PENTYLENE GLYCOL; HYDROXYETHYL CELLULOSE (100 MPA.S AT 2%); GLYCERIN; LONICERA JAPONICA FLOWER; ISOPROPYL ALCOHOL; LONICERA CAPRIFOLIUM FLOWER; DIMETHICONE; PEG-120 GLYCERYL STEARATE; TEA TREE OIL; .ALPHA.-BISABOLOL, (+)-; PEG-100 STEARATE; WATER; DICAPRYLYL CARBONATE; CETYL ALCOHOL; .ALPHA.-TOCOPHEROL ACETATE, D-; HYDROXYPHENYL PROPAMIDOBENZOIC ACID; STEARIC ACID; HYDROXYETHYL ACRYLATE/SODIUM ACRYLOYLDIMETHYL TAURATE COPOLYMER (45000 MPA.S AT 1%); CAPRYLYL GLYCOL; MAGNOLIA OFFICINALIS BARK; HEXYLENE GLYCOL; PHENOXYETHANOL; ETHYLHEXYLGLYCERIN; SUNFLOWER OIL; SQUALANE

Anna Guance MD Miracle Cream The Pimple Cream

Active Ingredient

Sulfur 10%

Purpose

Acne Treatment

WARNINGS

For external use only.

When using this product

- skin irritation and dryness is more likely to occur if you use another topical acne medication at the same time.
- if irritation occurs, only use one topical acne medication at a time.
- avoid contact with eyes. If contact occurs, flush thoroughly with water.
- apply only to areas with acne.

Stop use and ask a doctor if skin irritation or redness develops.

Keep out of reach of children. If swallowed, get medical help or contact a Poison Control Center right away.

Uses

- For Treatment of acne

Directions

- clean the skin thoroughly before applying this product
- cover the entire affected area with a thin layer one to two times daily
- because excessive drying of the skin may occur, start with one application daily then gradually increase to two times daily if needed

or as directed by a doctor.

- if bothersome dryness or peeling occurs, reduce application to once a day or every other day
- Sensitivity Test for New User. Apply product sparingly to one or two small affected areas during the first 3 days. If no discomforts occurs, follow directions stated above.

Other information Store at 68°F- 77°F (20°C- 25°C).

INACTIVE INGREDIENT

Inactive ingredients Water (Aqua), Helianthus Annuus (Sunflower) Seed Oil, Dicaprylyl Carbonate, Acacia Senegal Gum, Squalane, Glycerin, Calamine, Shea Butter, Glycerides, Dimethicone, Cetearyl Alcohol, Glyceryl Stearate, PEG-100, Stearane, Melaleuca Alternifolia (Tea Tree) Leaf Oil, Bisabolol, Tocopheryl Acetate, Magnolia Officinalis Bark Extract, Hydroxyphenyl Propamidobenzoic Acid, Stearic Acid, Ethylhexylglycerin, Hexylene Glycol, Hydroxyethyl Acrylate/Sodium Acryloyldimethyl Taurate Copolymer, Ceteareth-20, Pentylene Glycol, Disodium EDTA, Butylene Glycol, Caprylyl Glycol, Penoxyethanol, Fragrance (Parfum)

Do not use on

- broken skin
- large areas of the skin

QUESTIONS

Call 818-324-4339 or visit www.miraclecreambybella.com